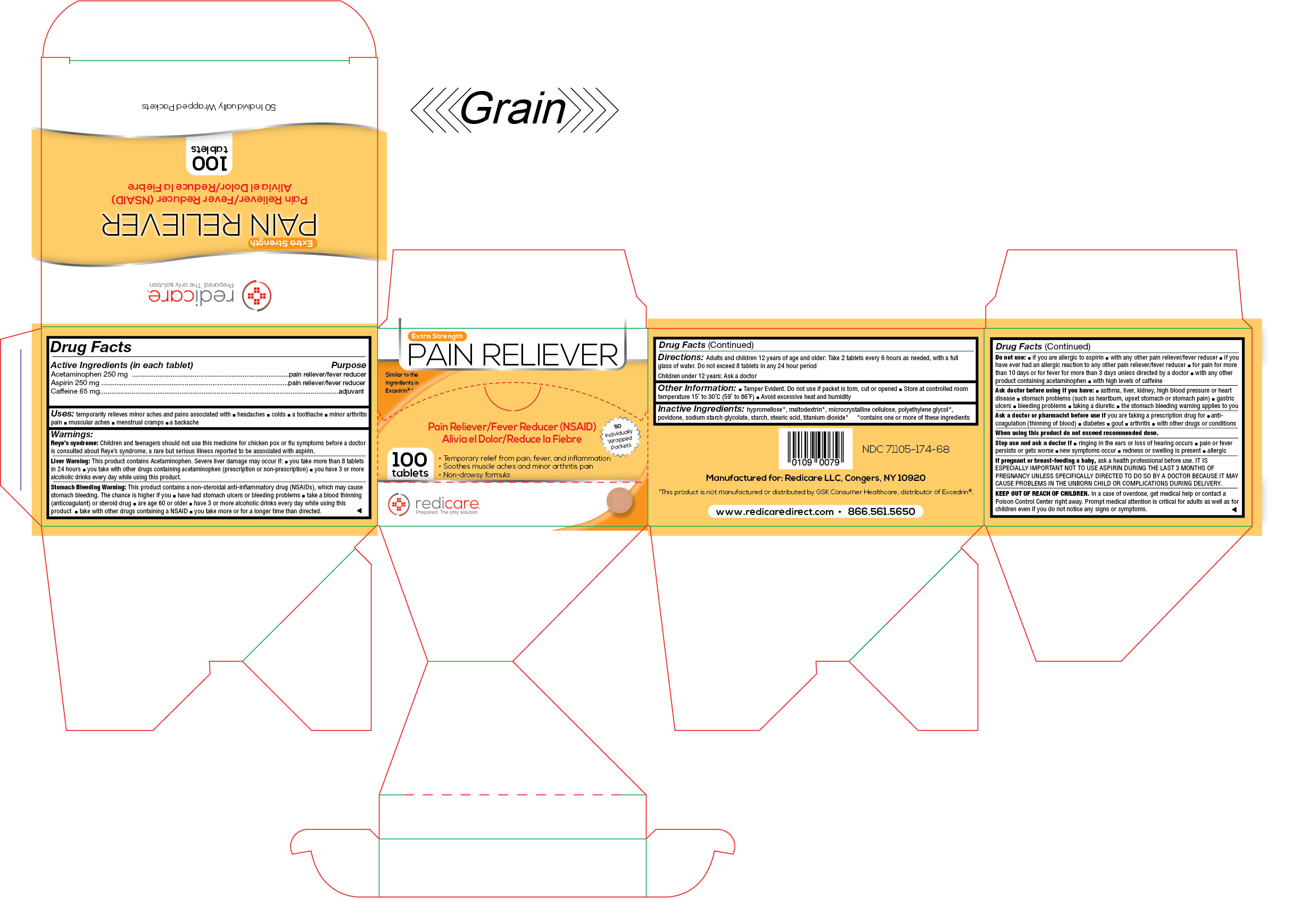 DRUG LABEL: Pain Reliever 2
NDC: 71105-174 | Form: TABLET
Manufacturer: Redicare LLC
Category: otc | Type: HUMAN OTC DRUG LABEL
Date: 20210702

ACTIVE INGREDIENTS: ACETAMINOPHEN 250 mg/1 1; ASPIRIN 250 mg/1 1; CAFFEINE 65 mg/1 1
INACTIVE INGREDIENTS: POVIDONE K30; STARCH, CORN; HYPROMELLOSE 2910 (3 MPA.S); HYPROMELLOSE 2910 (6 MPA.S); HYPROMELLOSE 2910 (50 MPA.S); SODIUM STARCH GLYCOLATE TYPE A POTATO; TITANIUM DIOXIDE; MICROCRYSTALLINE CELLULOSE; POLYETHYLENE GLYCOL 400; STEARIC ACID; MALTODEXTRIN

Advanced Pain Reliever

Active Ingredients (in each tablet)

Acetaminophen 250 mg

Aspirin 250 mg

Caffeine 65 mg

Purpose

pain reliever/fever reducer, adjuvant

Uses:

temporarily relieves minor aches and pains associated with ■ headaches ■ colds ■ a toothache ■ minor arthritis pain ■ muscular aches ■ menstrual cramps ■ a backache

Warnings:

Reye’s syndrome: Children and teenagers should not use this medicine for chickenpox or flu symptoms before a doctor is consulted about Reye’s syndrome, a rare but serious illness reported to be associated with aspirin.

Liver Warning

This product contains Acetaminophen. Severe liver damage may occur if: ■ you take more than 8 tablets in 24 hours ■ you take with other drugs containing acetaminophen (prescription or non-prescription) ■ you have 3 or more alcoholic drinks every day while using this product.

Stomach Bleeding Warning:

This product contains a non-steroidal anti-inflammatory drug (NSAIDs), which may cause stomach bleeding. The chance is higher if you ■ have had stomach ulcers or bleeding problems ■ take a blood-thinning (anticoagulant) or steroid drug ■ are age 60 or older ■ have 3 or more alcoholic drinks every day while using this product ■ take with other drugs containing an NSAID ■ you take more or for a longer time than directed.

Do not use:

■ if you are allergic to aspirin ■ with any other pain reliever/fever reducer ■ if you have ever had an allergic reaction to any other pain reliever/fever reducer ■ for pain for more than 10 days or for fever for more than 3 days unless directed by a doctor ■ with any other product containing acetaminophen ■ with large amounts of caffeinated products

Ask a doctor before use if you have:

■ asthma, liver, kidney, high blood pressure or heart disease ■ stomach problems (such as heartburn, upset or painful stomach) ■ gastric ulcers ■ bleeding problems ■ taking a diuretic ■ or if the stomach bleeding warning applies to you

Ask a doctor or pharmacist before use if

you are taking a prescription drug for ■ anticoagulation (thinning of blood) ■ diabetes ■ gout ■ arthritis ■ with other drugs or conditions

When using this product

do not exceed the recommended dose.

Stop use and ask a doctor if:

■ ringing in the ears or loss of hearing occurs ■ pain or fever persists or worsens ■ new symptoms occur ■ allergic reaction, redness or swelling is present

If pregnant or breast-feeding a baby,

ask a health professional before use. IT IS ESPECIALLY IMPORTANT NOT TO USE ASPIRIN DURING THE LAST 3 MONTHS OF PREGNANCY UNLESS SPECIFICALLY DIRECTED TO DO SO BY A DOCTOR BECAUSE IT MAY CAUSE PROBLEMS IN THE UNBORN CHILD OR COMPLICATIONS DURING DELIVERY.

KEEP OUT OF REACH OF CHILDREN.

In case of overdose, get medical help or contact a Poison Control Center right away. Prompt medical attention is critical for adults as well as for children even if you do not notice any signs or symptoms.

Directions:

Adults and children 12 years of age and older: Take 2 tablets every 6 hours as needed, with a full glass of water. Do not exceed 8 tablets in any 24 hour period

Children under 12 years: Ask a doctor

Other Information:

■ Tamper Evident. Do not use if a packet is torn, cut or opened ■ Store at controlled room temperature 15˚ to 30˚C (59˚ to 86˚F) ■ Avoid excessive heat and humidity

Inactive Ingredients:

hypromellose*, maltodextrin*, microcrystalline cellulose, polyethylene glycol*, povidone, sodium starch glycolate, starch, stearic acid, titanium dioxide*

*contains one or more of these ingredients